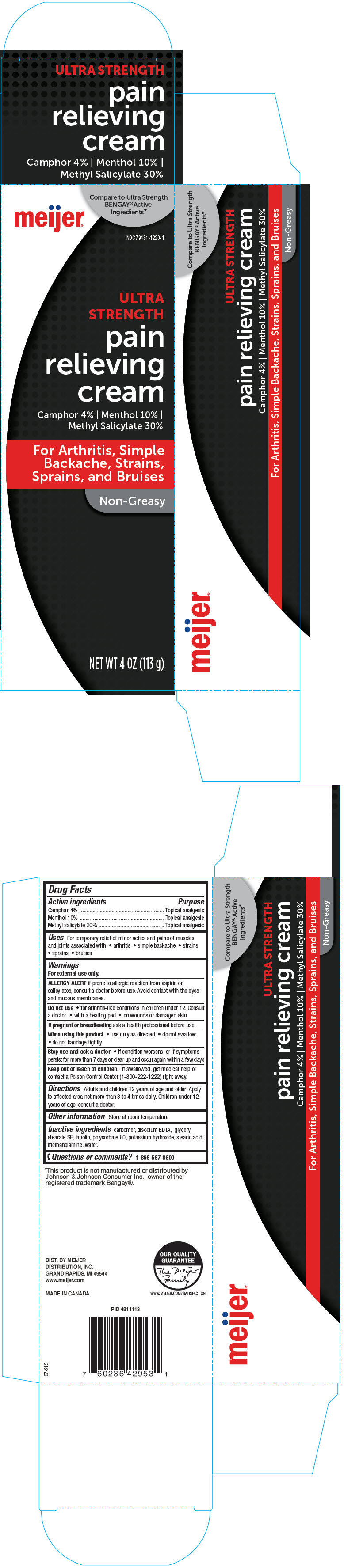 DRUG LABEL: Meijer Ultra Strength Pain Relieving
NDC: 79481-1220 | Form: CREAM
Manufacturer: Meijer Distribution, Inc
Category: otc | Type: HUMAN OTC DRUG LABEL
Date: 20241115

ACTIVE INGREDIENTS: CAMPHOR (SYNTHETIC) 40 mg/1 g; MENTHOL, UNSPECIFIED FORM 100 mg/1 g; METHYL SALICYLATE 300 mg/1 g
INACTIVE INGREDIENTS: CARBOMER HOMOPOLYMER, UNSPECIFIED TYPE; EDETATE DISODIUM; Glyceryl Stearate SE; Lanolin; Polysorbate 80; Potassium Hydroxide; Stearic Acid; TROLAMINE; Water

Meijer® Ultra Strength Pain Relieving Cream
Topical Analgesic

Drug Facts

ACTIVE INGREDIENT

Active ingredients | Purpose
Camphor 4% | Topical analgesic
Menthol 10% | Topical analgesic
Methyl salicylate 30% | Topical analgesic

Uses

For temporary relief of minor aches and pains of muscles and joints associated with

- arthritis
- simple backache
- strains
- sprains
- bruises

Warnings

For external use only.

ALLERGY ALERT if prone to allergic reaction from aspirin or salicylates, consult a doctor before use. Avoid contact with the eyes and mucous membranes.

Do not use

- for arthritis-like conditions in children under 12. Consult a doctor.
- with a heating pad
- on wounds or damaged skin

PREGNANCY OR BREAST FEEDING

If pregnant or breastfeeding ask a health professional before use.

When using this product

- use only as directed
- do not swallow
- do not bandage tightly

Stop use and ask a doctor

- if condition worsens, or if symptoms persist for more than 7 days or clear up and occur again within a few days

Keep out of reach of children. If swallowed, get medical help or contact a Poison Control Center (1-800-222-1222) right away.

Directions

Adults and children 12 years of age and older: Apply to affected area not more than 3 to 4 times daily. Children under 12 years of age: consult a doctor.

Other information

Store at room temperature

Inactive ingredients

carbomer, disodium EDTA, glyceryl stearate SE, lanolin, polysorbate 80, potassium hydroxide, stearic acid, triethanolamine, water.

Questions or comments?

1-866-567-8600

DIST. BY MEIJER
DISTRIBUTION, INC.
GRAND RAPIDS, MI 49544

PRINCIPAL DISPLAY PANEL - 113 g Tube Carton

meijer®

Compare to Ultra Strength
BENGAY® Active
Ingredients*

NDC 79481-1220-1

ULTRA
STRENGTH

pain
relieving
cream

Camphor 4% | Menthol 10% |
Methyl Salicylate 30%

For Arthritis, Simple
Backache, Strains,
Sprains, and Bruises

Non-Greasy

NET WT 4 OZ (113 g)